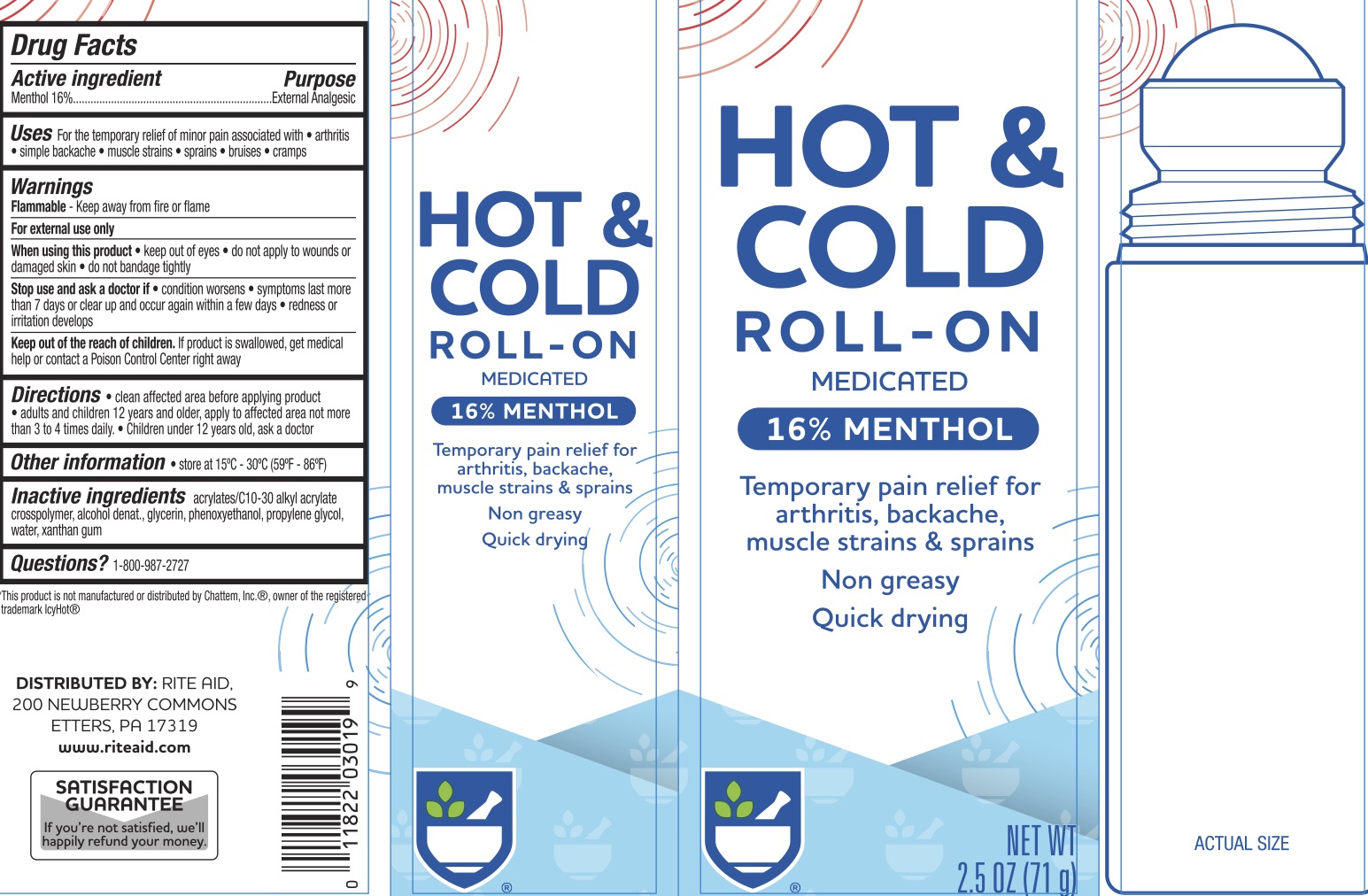 DRUG LABEL: Rite Aid Hot and Cold Roll On
NDC: 11822-1015 | Form: LIQUID
Manufacturer: Rite Aid
Category: otc | Type: HUMAN OTC DRUG LABEL
Date: 20241215

ACTIVE INGREDIENTS: MENTHOL 16 g/100 g
INACTIVE INGREDIENTS: PHENOXYETHANOL; CARBOMER INTERPOLYMER TYPE B (ALLYL PENTAERYTHRITOL CROSSLINKED); GLYCERIN; WATER; ALCOHOL; PROPYLENE GLYCOL; XANTHAN GUM

Rite Aid Hot & Cold Roll-on

ACTIVE INGREDIENT

Menthol 16%

PURPOSE

External Analgesic

INDICATIONS AND USAGE

For the temporary relief of minor pain associated with arthritis, simple backache, muscle strains, sprains, bruises, and cramps.

WARNINGS

Flammable--keep away from fire or flame.

For external use only.

When using this product keep out of eyes, do not apply to wounds or damaged skin, do not bandage tightly.

Stop use and ask a doctor if condition worsens, symptoms last more than 7 days or clear and occur again within a few days, and redness or irritation develops.

KEEP OUT OF REACH OF CHILDREN

If product is swallowed, get medical help or contact a Poison Control Center right away.

DOSAGE AND ADMINISTRATION

Clean affected area before applying product • adults and children 12 years and older, apply to affected area not more
than 3 to 4 times daily. • Children under 12 years old, ask a doctor

INACTIVE INGREDIENT

Acrylates/C10-30 alkyl acrylate crosspolymer, alcohol denat., glycerin, phenoxyethanol, propylene glycol, water, xanthan gum